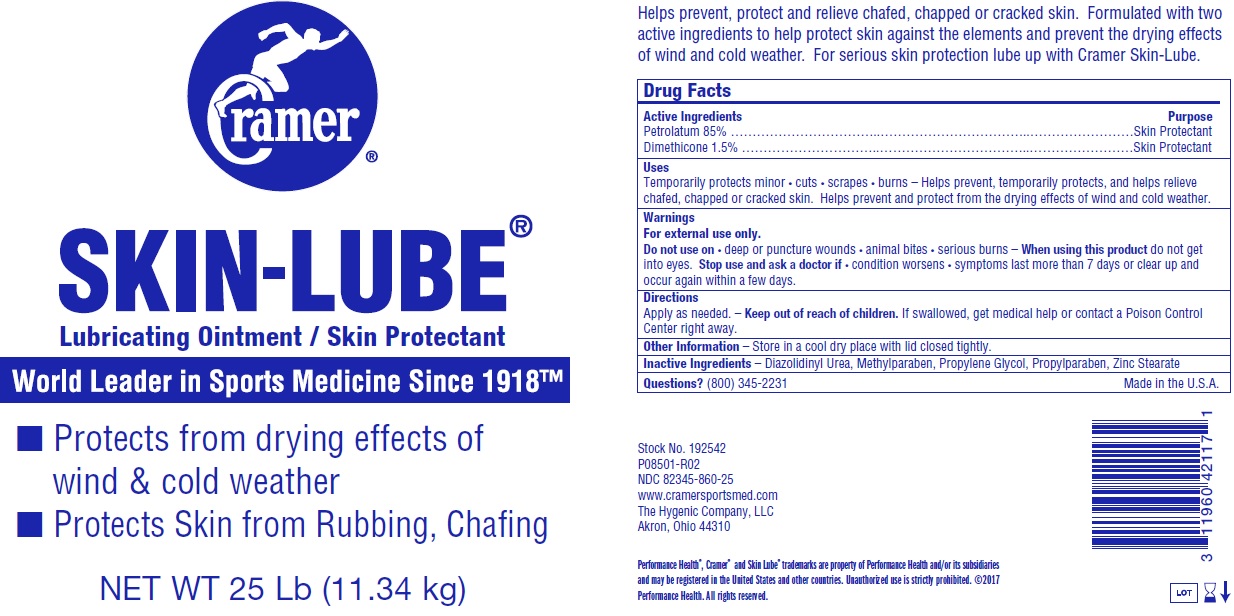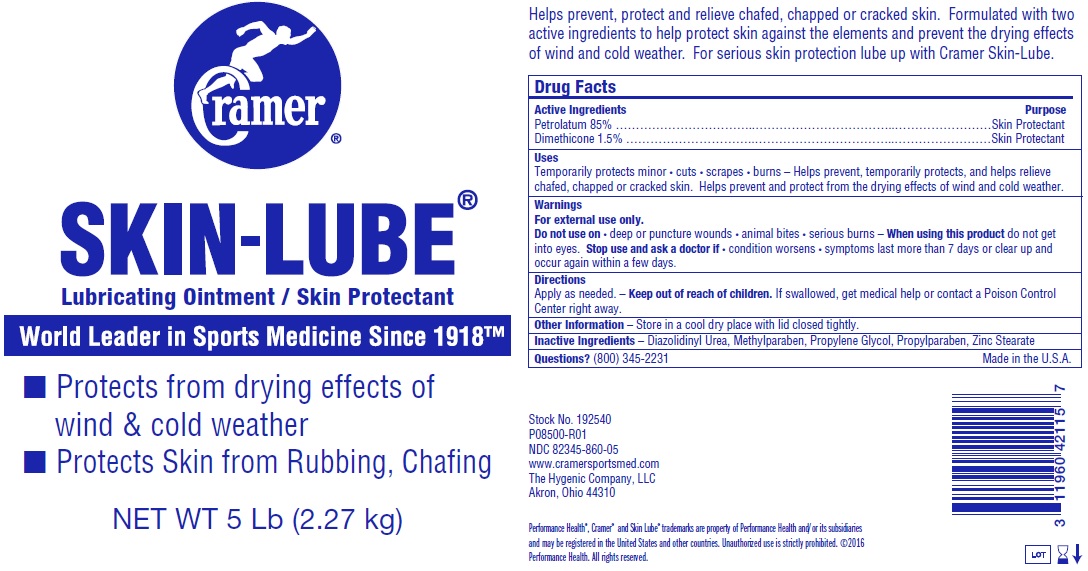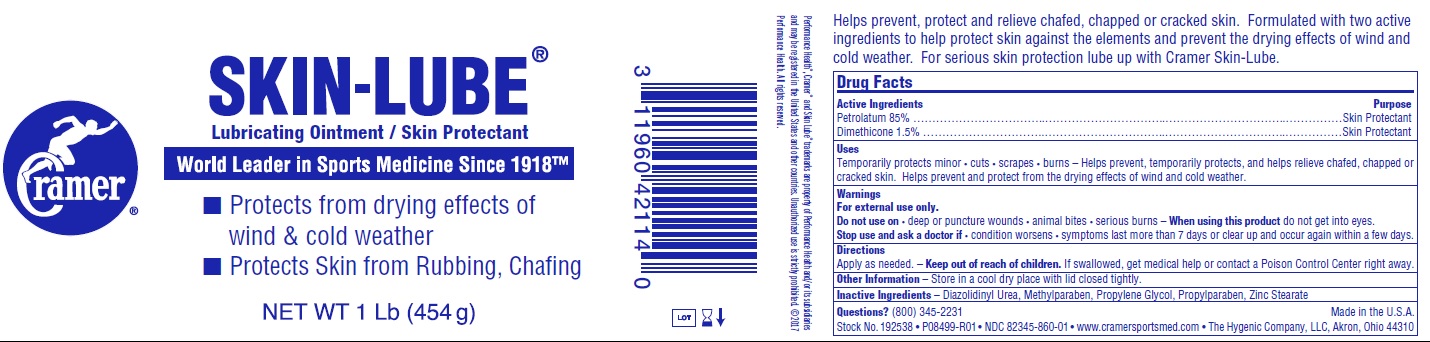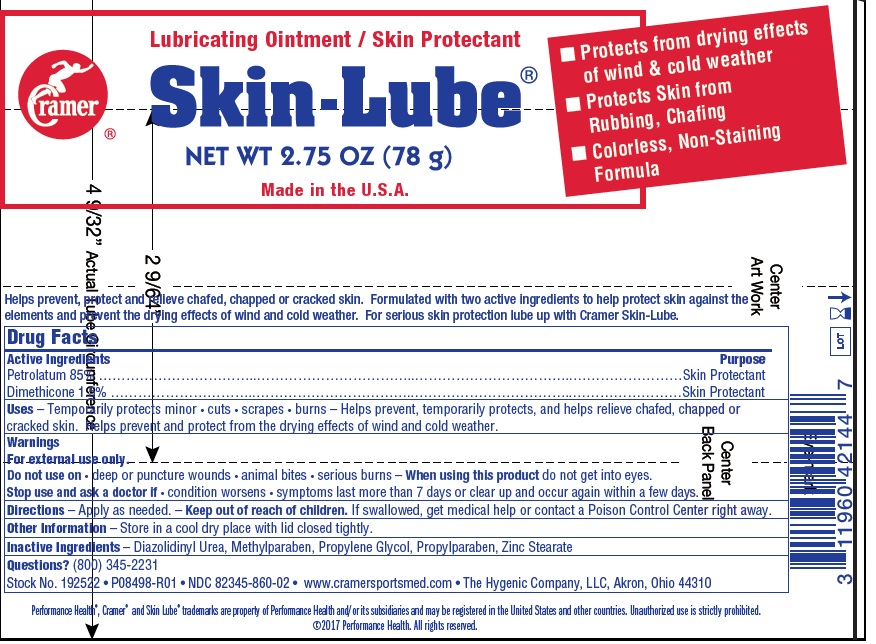 DRUG LABEL: Skin-lube
NDC: 82345-860 | Form: OINTMENT
Manufacturer: The Hygenic Company, LLC.
Category: otc | Type: HUMAN OTC DRUG LABEL
Date: 20231105

ACTIVE INGREDIENTS: PETROLATUM 850 mg/1 g; DIMETHICONE 15 mg/1 g
INACTIVE INGREDIENTS: DIAZOLIDINYL UREA; METHYLPARABEN; PROPYLENE GLYCOL; PROPYLPARABEN; ZINC STEARATE

Skin-lube

Active Ingredients

Petrolatum 85%

Dimethicone 1.5%

Purpose

Skin Protectant

Uses

Temporarily protects minor • cuts • scrapes • burns – Helps prevent, temporarily protects, and helps relieve chafed, chapped or cracked skin. Helps prevent and protect from the drying effects of wind and cold weather.

Warnings

For external use only.

Do not use on

• deep or puncture wounds • animal bites • serious burns

When using this product

do not get into eyes.

Stop use and ask a doctor if

• condition worsens • symptoms last more than 7 days or clear up and occur again within a few days.

Keep out of reach of children.

If swallowed, get medical help or contact a Poison Control Center right away.

Directions

Apply as needed.

Other Information

– Store in a cool dry place with lid closed tightly.

Inactive Ingredients

– Diazolidinyl Urea, Methylparaben, Propylene Glycol, Propylparaben, Zinc Stearate

Questions?

(800) 345-2231